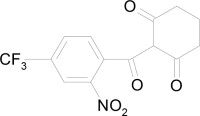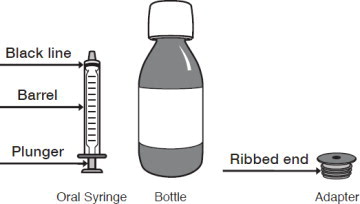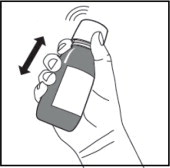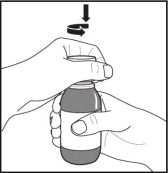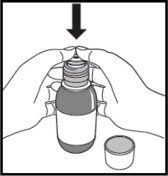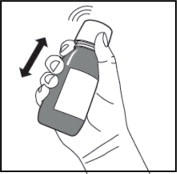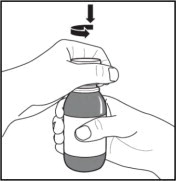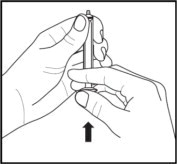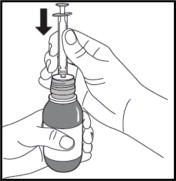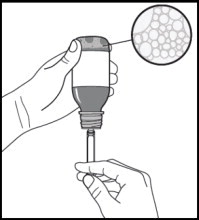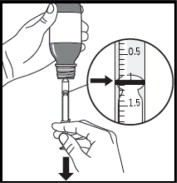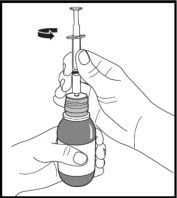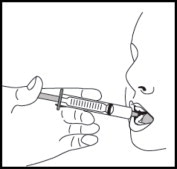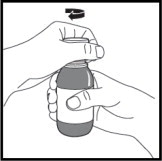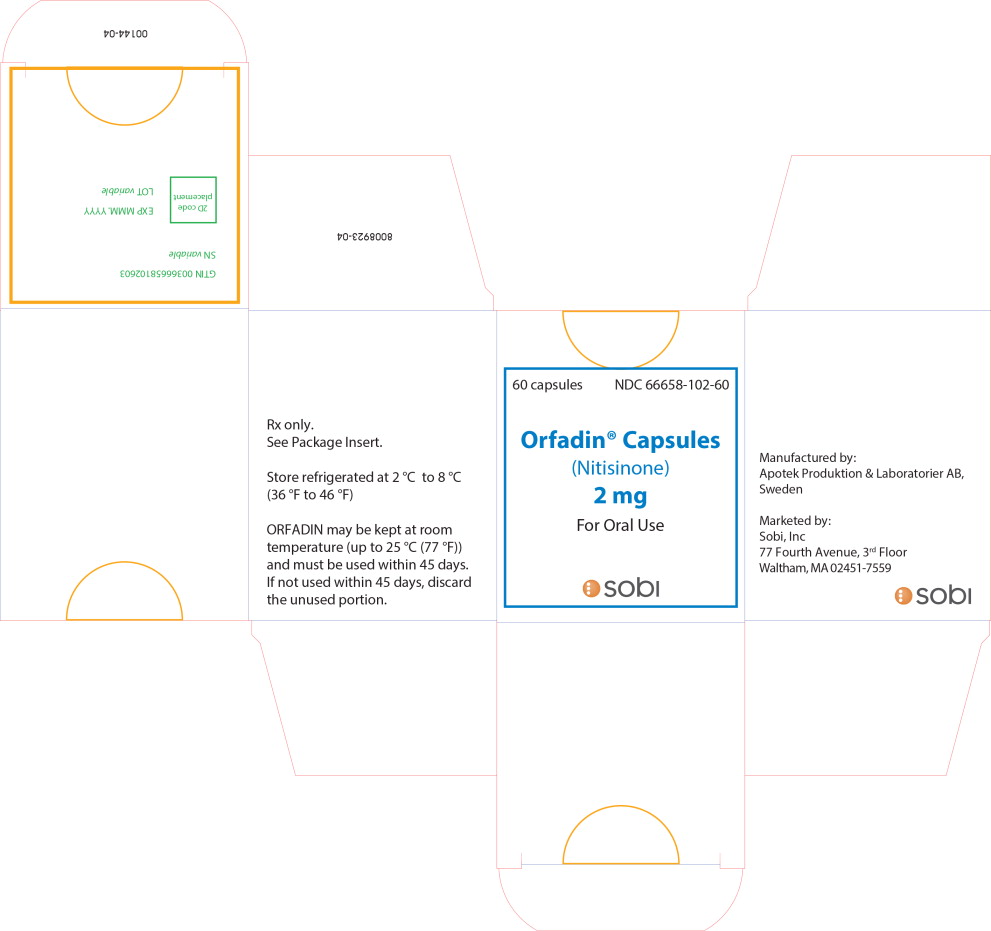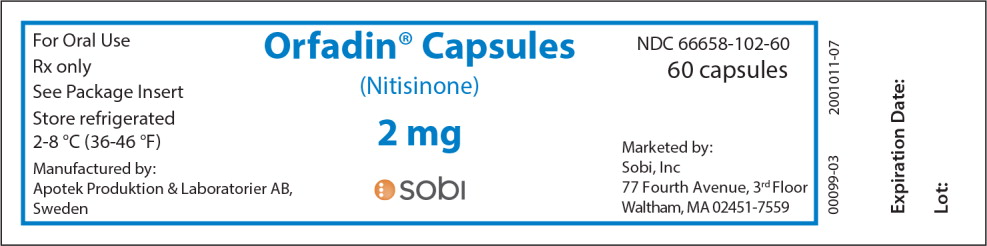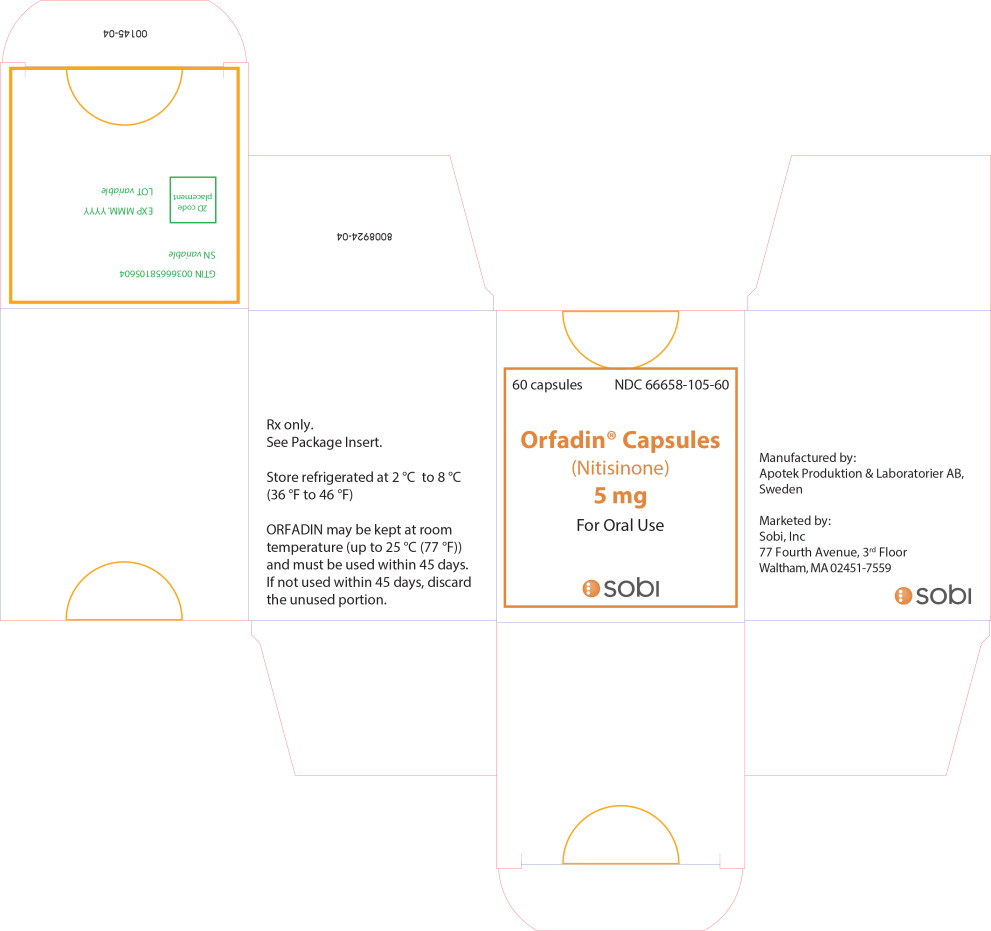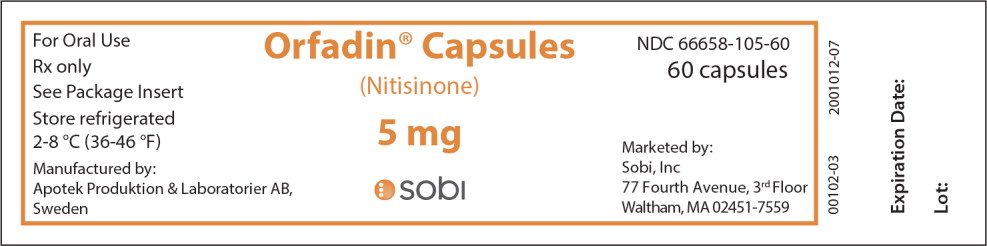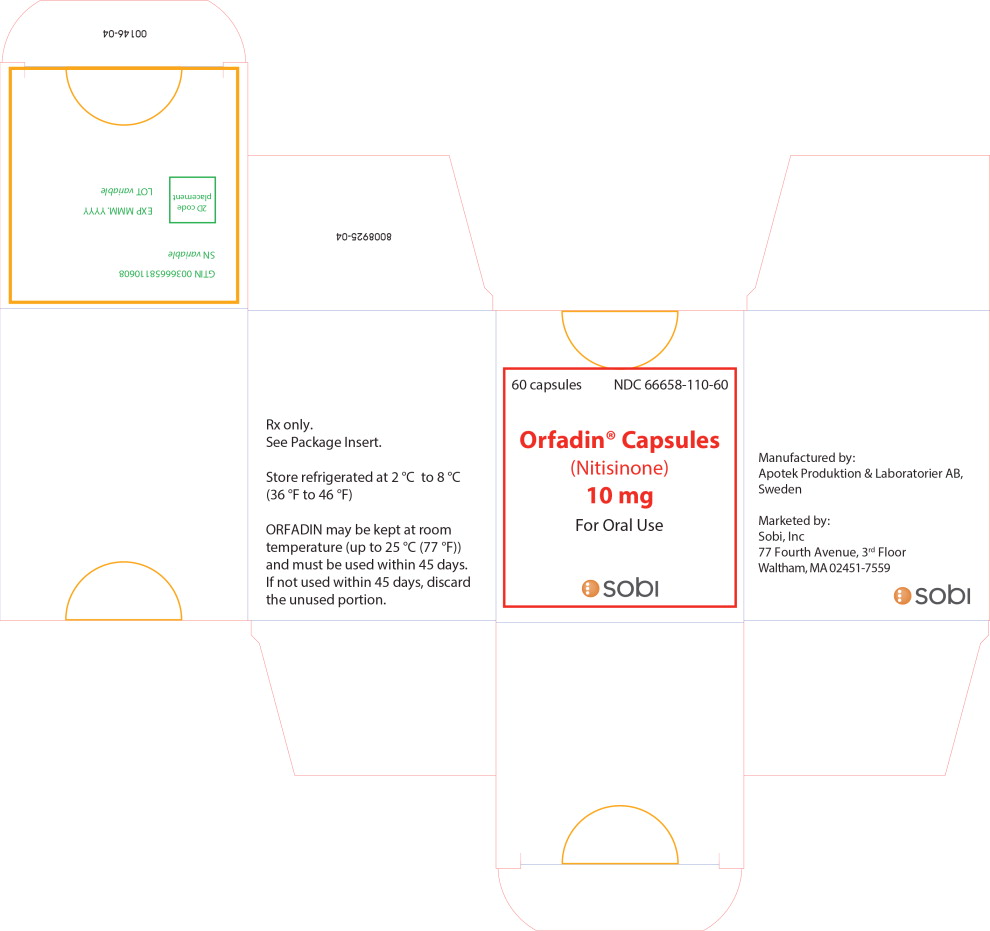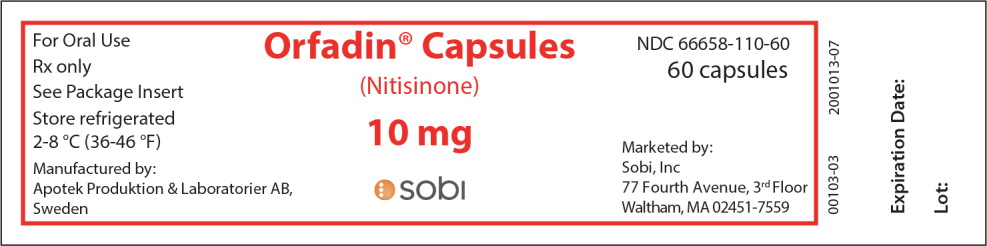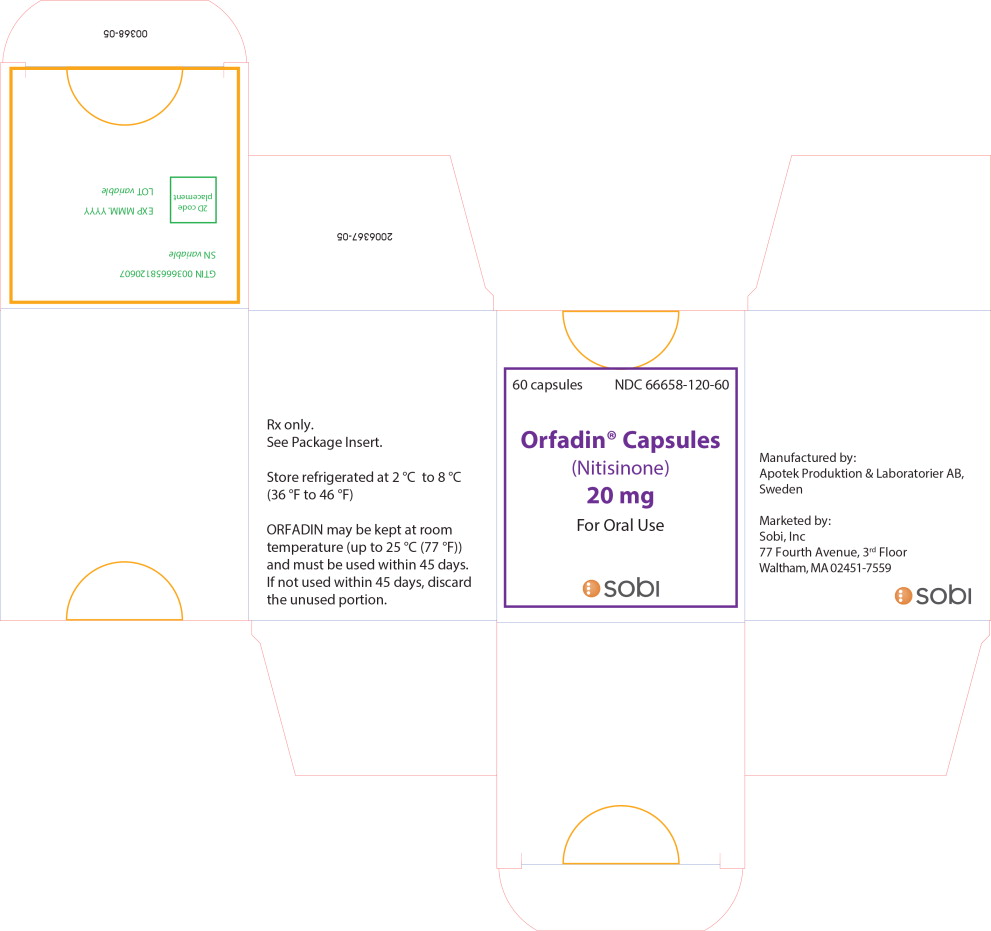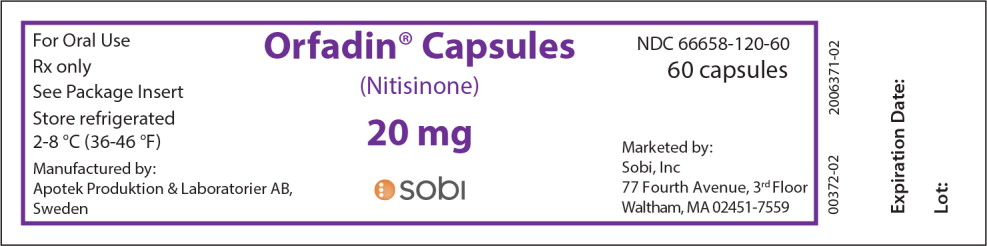 DRUG LABEL: Orfadin
NDC: 66658-102 | Form: CAPSULE
Manufacturer: SWEDISH ORPHAN BIOVITRUM AB (PUBL)
Category: prescription | Type: HUMAN PRESCRIPTION DRUG LABEL
Date: 20211130

ACTIVE INGREDIENTS: nitisinone 2 mg/1 1
INACTIVE INGREDIENTS: STARCH, CORN; GELATIN; TITANIUM DIOXIDE

HIGHLIGHTS OF PRESCRIBING INFORMATION

These highlights do not include all the information needed to use ORFADIN safely and effectively. See full prescribing information for ORFADIN.
ORFADIN® (nitisinone) capsules, for oral use
ORFADIN® (nitisinone) oral suspension
Initial U.S. Approval: 2002

RECENT MAJOR CHANGES

Warnings and Precautions (5.1) | 05/2019

1 INDICATIONS AND USAGE

ORFADIN is a hydroxy-phenylpyruvate dioxygenase inhibitor indicated for the treatment of adult and pediatric patients with hereditary tyrosinemia type 1 (HT-1) in combination with dietary restriction of tyrosine and phenylalanine. (1)

2 DOSAGE AND ADMINISTRATION

Recommended Dosage (2.1):

- The recommended starting dosage is 0.5 mg/kg orally twice daily.
- In patients 5 years of age and older who have undetectable serum and urine succinylacetone concentrations after a minimum of 4 weeks on a stable dosage of nitisinone, the total daily dose may be given once daily.
- Titrate the dosage based on biochemical and/or clinical response, as described in the full prescribing information.
- The maximum total daily dosage is 2 mg/kg orally.

Preparation and Administration Instructions (2.2):

- For instructions on preparing, measuring and administering the oral suspension, see the full prescribing information.
- Maintain dietary restriction of tyrosine and phenylalanine
- Take ORFADIN capsules at least one hour before, or two hours after a meal
- For patients who have difficulties swallowing capsules and who are intolerant to the oral suspension, the capsules may be opened and the contents suspended in a small amount of water, formula or apple sauce immediately before use.

Take ORFADIN oral suspension without regard to meals.

3 DOSAGE FORMS AND STRENGTHS

- Capsules: 2 mg, 5 mg, 10 mg, 20 mg. (3)
- Oral suspension: 4 mg/mL (3)

4 CONTRAINDICATIONS

None (4)

5 WARNINGS AND PRECAUTIONS

- Elevated Plasma Tyrosine Levels, Ocular Symptoms, Developmental Delay and Hyperkeratotic Plaques: Inadequate restriction of tyrosine and phenylalanine intake can lead to elevations in plasma tyrosine, which at levels above 500 micromol/L can result in symptoms, intellectual disability and developmental delay or painful hyperkeratotic plaques on the soles and palms; do not adjust ORFADIN dosage in order to lower the plasma tyrosine concentration. Obtain slit-lamp examination prior to treatment, regularly during treatment; Reexamine patients if symptoms develop or tyrosine levels are > 500 micromol/L. Assess plasma tyrosine levels in patients with an abrupt change in neurologic status. (5.1)
- Leukopenia and Severe Thrombocytopenia: Monitor platelet and white blood cell counts. (5.2)
- Risk of Adverse Reactions Due to Glycerol Content of ORFADIN Oral Suspension: Doses of 20 mL of ORFADIN oral suspension may cause headache, upset stomach and diarrhea due to the glycerol content. Consider switching patients to ORFADIN capsules. (5.3)

6 ADVERSE REACTIONS

Most common adverse reactions (>1%) are elevated tyrosine levels, thrombocytopenia, leukopenia, conjunctivitis, corneal opacity, keratitis, photophobia, eye pain, blepharitis, cataracts, granulocytopenia, epistaxis, pruritus, exfoliative dermatitis, dry skin, maculopapular rash and alopecia. (6.1)

To report SUSPECTED ADVERSE REACTIONS, contact Swedish Orphan Biovitrum at 1-866-773-5274 or FDA at 1-800-FDA-1088 or www.fda.gov/medwatch.

7 DRUG INTERACTIONS

- CYP2C9 Substrates: Increased systemic exposure of these co-administered drugs; reduce the dosage. Additional dosage adjustments may be needed to maintain therapeutic drug concentrations for narrow therapeutic index drugs. (7)
- OAT1/OAT3 Substrates: Increased systemic exposure of these co-administered drugs; monitor for potential adverse reactions. (7)

FULL PRESCRIBING INFORMATION

1 INDICATIONS AND USAGE

ORFADIN® is indicated for the treatment of adult and pediatric patients with hereditary tyrosinemia type 1 (HT-1) in combination with dietary restriction of tyrosine and phenylalanine.

2 DOSAGE AND ADMINISTRATION

2.1 Dosage

Starting Dosage

The recommended starting dosage of ORFADIN is 0.5 mg/kg administered orally twice daily.

Maintenance Regimen

In patients 5 years of age and older who have undetectable serum and urine succinylacetone concentrations after a minimum of 4 weeks on a stable dosage of nitisinone, the total daily dose of ORFADIN may be given once daily (e.g., 1 to 2 mg/kg once daily) [see Clinical Pharmacology (12.2)].

Dosage Titration

Titrate the dosage in each individual patient based on biochemical and/or clinical response.

- Monitor plasma and/or urine succinylacetone concentrations, liver function parameters and alpha-fetoprotein levels.
- If succinylacetone is still detectable in blood or urine 4 weeks after the start of nitisinone treatment, increase the nitisinone dosage to 0.75 mg/kg twice daily. A maximum total daily dosage of 2 mg/kg may be needed based on the evaluation of all biochemical parameters.
- If the biochemical response is satisfactory (undetectable blood and/or urine succinylacetone), the dosage should be adjusted only according to body weight gain and not according to plasma tyrosine levels.
- During initiation of therapy, when switching from twice daily to once daily dosing, or if there is a deterioration in the patient's condition, it may be necessary to follow all available biochemical parameters more closely (i.e. plasma and/or urine succinylacetone, urine 5-aminolevulinate (ALA) and erythrocyte porphobilinogen (PBG)-synthase activity).
- Maintain plasma tyrosine levels below 500 micromol/L by dietary restriction of tyrosine and phenylalanine intake [see Warnings and Precautions (5.1)]. In patients who develop plasma tyrosine levels above 500 micromol/L, assess dietary tyrosine and phenylalanine intake. Do not adjust the ORFADIN dosage in order to lower the plasma tyrosine concentration.

2.2 Preparation and Administration Instructions

Preparation of the Oral Suspension

The oral suspension will be dispensed with an oral syringe of appropriate size and a bottle adaptor provided by a pharmacist or other healthcare provider.

Preparing a Bottle Without the Adapter Already Inserted:

- Store the bottle in the refrigerator prior to first use.
- Remove the bottle from the refrigerator. Calculate 60 days from when the bottle is removed from the refrigerator. Write this date as the “Discard after” date on the bottle label.
- Allow the bottle to warm to room temperature (30 to 60 minutes).
- Shake the bottle vigorously for at least 20 seconds until the solid cake at the bottom of the bottle is completely dispersed. Check that there are no particles left at the bottom of the bottle. Foam will form in the bottle.
- Insert the bottle adapter.

Preparing a Bottle With the Adapter Inserted:

- Shake the bottle vigorously for at least 5 seconds. Check that there are no particles left at the bottom of the bottle. Foam will form in the bottle.

Measuring and Administering the Dose

Once the bottle is prepared with the adapter:

1. Use the oral syringe to measure the dose.
2. Keep the bottle upright and insert the oral syringe into the adapter.
3. Carefully turn the bottle upside down with the oral syringe in place. Wait for the foam to rise to the top of the bottle.
4. Pull back on the syringe plunger to withdraw the dose.
5. Leave the syringe in the adapter and turn the bottle upright.
6. Remove the syringe from the adapter by gently twisting it out of the bottle.
7. Dispense the dose into the patient's mouth.
8. Do not remove the bottle adapter.
9. Store the bottle at room temperature (not above 25°C).

Administration of ORFADIN Capsules and Oral Suspension

- Maintain dietary restriction of tyrosine and phenylalanine when taking ORFADIN.
- Capsules: Take at least one hour before, or two hours after a meal [see Clinical Pharmacology (12.3)]. For patients who have difficulty swallowing the capsules and who are intolerant to the oral suspension [see Warnings and Precautions (5.3)], the capsules may be opened and the contents suspended in a small amount of water, formula or apple sauce immediately before use.
- Oral suspension: Take without regard to meals [see Clinical Pharmacology (12.3)].

3 DOSAGE FORMS AND STRENGTHS

- Capsules: 2 mg, 5 mg, 10 mg and 20 mg white capsules imprinted with “NTBC” followed by “2 mg”, “5 mg”, “10 mg” or ”20 mg”, indicating the actual amount of nitisinone in each capsule.
- Oral suspension: 4 mg/mL, a white, slightly viscous opaque suspension.

4 CONTRAINDICATIONS

None.

5 WARNINGS AND PRECAUTIONS

5.1 Elevated Plasma Tyrosine Levels, Ocular Symptoms, Developmental Delay and Hyperkeratotic Plaques

Nitisinone is an inhibitor of 4-hydroxyphenyl-pyruvate dioxygenase, an enzyme in the tyrosine metabolic pathway [see Clinical Pharmacology (12.1)]. Therefore, treatment with ORFADIN may cause an increase in plasma tyrosine levels in patients with HT-1. Maintain concomitant reduction in dietary tyrosine and phenylalanine while on ORFADIN treatment. Do not adjust ORFADIN dosage in order to lower the plasma tyrosine concentration. Maintain plasma tyrosine levels below 500 micromol/L. Inadequate restriction of tyrosine and phenylalanine intake can lead to elevations in plasma tyrosine levels and levels greater than 500 micromol/L may lead to the following:

- Ocular signs and symptoms including corneal ulcers, corneal opacities, keratitis, conjunctivitis, eye pain, and photophobia have been reported in patients treated with ORFADIN [see Adverse Reactions (6.1)]. In a clinical study in a non HT-1 population without dietary restriction and reported tyrosine levels >500 micromol/L both symptomatic and asymptomatic keratopathies have been observed. Therefore, perform a baseline ophthalmologic examination including slit-lamp examination prior to initiating ORFADIN treatment and regularly thereafter. Patients who develop photophobia, eye pain, or signs of inflammation such as redness, swelling, or burning of the eyes or tyrosine levels are > 500 micromol/L during treatment with ORFADIN should undergo slit-lamp reexamination and immediate measurement of the plasma tyrosine concentration.
- Variable degrees of intellectual disability and developmental delay. In patients treated with ORFADIN who exhibit an abrupt change in neurologic status, perform a clinical laboratory assessment including plasma tyrosine levels.
- Painful hyperkeratotic plaques on the soles and palms

In patients with HT-1 treated with dietary restrictions and ORFADIN who develop elevated plasma tyrosine levels, assess dietary tyrosine and phenylalanine intake.

5.2 Leukopenia and Severe Thrombocytopenia

In clinical trials, patients treated with ORFADIN and dietary restriction developed transient leukopenia (3%), thrombocytopenia (3%), or both (1.5%) [see Adverse Reactions (6.1)]. No patients developed infections or bleeding as a result of the episodes of leukopenia and thrombocytopenia. Monitor platelet and white blood cell counts during ORFADIN therapy.

5.3 Risk of Adverse Reactions Due to Glycerol Content of ORFADIN Oral Suspension

Oral doses of glycerol of 10 grams or more have been reported to cause headache, upset stomach and diarrhea. ORFADIN oral suspension contains 500 mg/mL of glycerol. Patients receiving more than 20 mL of ORFADIN oral suspension (10 grams glycerol) as a single dose are at increased risk of these adverse reactions. Consider switching patients who are unable to tolerate the oral suspension to ORFADIN capsules.

6 ADVERSE REACTIONS

6.1 Clinical Trials Experience

Because clinical trials are conducted under widely varying conditions, adverse reaction rates observed in the clinical trials of a drug cannot be directly compared to rates in the clinical trials of another drug and may not reflect the rates observed in clinical practice.

ORFADIN was studied in one open-label, uncontrolled study of 207 patients with HT-1, ages 0 to 22 years at enrollment (median age 9 months), who were diagnosed with HT-1 by the presence of succinylacetone in the urine or plasma. The starting dose of ORFADIN was 0.3 to 0.5 mg/kg twice daily, and the dose was increased in some patients to 1 mg/kg twice daily based on weight, biochemical, and enzyme markers. The recommended starting dosage of ORFADIN is 0.5 mg/kg twice daily [see Dosage and Administration (2.1)]. Median duration of treatment was 22 months (range 0.1 to 80 months).

The most serious adverse reactions reported during ORFADIN treatment were thrombocytopenia, leukopenia, porphyria, and ocular/visual complaints associated with elevated tyrosine levels [see Warnings and Precautions (5.1, 5.2)]. Fourteen patients experienced ocular/visual events. The duration of the symptoms varied from 5 days to 2 years. Six patients had thrombocytopenia, three of which had platelet counts 30,000/microL or lower. In 4 patients with thrombocytopenia, platelet counts gradually returned to normal (duration up to 47 days) without change in ORFADIN dose. No patients developed infections or bleeding as a result of the episodes of leukopenia and thrombocytopenia.

Patients with HT- 1 are at increased risk of developing porphyric crises, hepatic neoplasms, and liver failure requiring liver transplantation. These complications of HT-1 were observed in patients treated with nitisinone for a median of 22 months during the clinical trial (liver transplantation 13%, liver failure 7%, malignant hepatic neoplasms 5%, benign hepatic neoplasms 3%, porphyria 1%).

The most common adverse reactions reported in the clinical trial are summarized in Table 1.

TABLE 1
Most Common Adverse Reactions in Patients with HT-1 Treated with Nitisinone*
Elevated tyrosine levels Leukopenia Thrombocytopenia Conjunctivitis Corneal opacity Keratitis Photophobia Eye pain Blepharitis Cataracts Granulocytopenia Epistaxis Pruritus Exfoliative dermatitis Dry skin Maculopapular rash Alopecia | >10% 3% 3% 2% 2% 2% 2% 1% 1% 1% 1% 1% 1% 1% 1% 1% 1%
*reported in at least 1% of patients

Adverse reactions reported in less than 1% of the patients, included death, seizure, brain tumor, encephalopathy, hyperkinesia, cyanosis, abdominal pain, diarrhea, enanthema, gastrointestinal hemorrhage, melena, elevated hepatic enzymes, liver enlargement, hypoglycemia, septicemia, and bronchitis.

7 DRUG INTERACTIONS

Nitisinone is a moderate CYP2C9 inhibitor, a weak CYP2E1 inducer and an inhibitor of OAT1/OAT3. Table 2 includes drugs with clinically important drug interactions when administered concomitantly with ORFADIN and instructions for preventing or managing them.

Table 2: Clinically Relevant Interactions Affecting Co-Administered Drugs
Sensitive CYP2C9 Substrates (e.g., celecoxib, tolbutamide) or CYP2C9 Substrates with a Narrow Therapeutic Index (e.g., phenytoin, warfarin)
Clinical Impact | Increased exposure of the co-administered drugs metabolized by CYP2C9. [see Clinical Pharmacology (12.3)]
Intervention | Reduce the dosage of the co-administered drugs metabolized by CYP2C9 drug by half. Additional dosage adjustments may be needed to maintain therapeutic drug concentrations for narrow therapeutic index drugs. See prescribing information for those drugs.
OAT1/OAT3 Substrates (e.g., adefovir, ganciclovir, methotrexate)
Clinical Impact | Increased exposure of the interacting drug [see Clinical Pharmacology (12.3)]
Intervention | Monitor for potential adverse reactions related to the co-administered drug.

8 USE IN SPECIFIC POPULATIONS

8.1 Pregnancy

Risk Summary

Limited available data with nitisinone use in pregnant women are not sufficient to determine a drug-associated risk of adverse developmental outcomes. Animal reproduction studies have been conducted for nitisinone. In these studies, nitisinone was administered to mice and rabbits during organogenesis with oral doses of nitisinone up to 20 and 8 times respectively, the recommended initial dose of 1 mg/kg/day. In mice, nitisinone caused incomplete skeletal ossification of fetal bones and decreased pup survival at doses 0.4 times the recommended initial dose, and increased gestational length at doses 4 times the recommended initial dose. In rabbits, nitisinone caused maternal toxicity and incomplete skeletal ossification of fetal bones at doses 1.6 times the recommended initial dose [see Data].

The background risk of major birth defects and miscarriage for the indicated population are unknown. In the U.S. general population, the estimated background risk of major birth defects and miscarriage in clinically recognized pregnancies is 2 to 4% and 15 to 20%, respectively.

Data

Animal Data

Reproduction studies have been performed in mice at oral doses of about 0.4, 4 and 20 times the recommended initial dose (1 mg/kg/day) and in rabbits at oral doses of about 1.6, 4 and 8 times the recommended initial dose based on the body surface area. In mice, nitisinone has been shown to cause incomplete skeletal ossification of fetal bones at 0.4, 4 and 20 times the recommended initial dose, increased gestational length at 4 and 20 times the recommended initial dose, and decreased pup survival at 0.4 times the recommended initial dose based on the body surface area. In rabbits, nitisinone caused incomplete skeletal ossification of fetal bones at 1.6, 4 and 8 times the recommended initial dose based on the body surface area.

8.2 Lactation

Risk Summary

There are no data on the presence of nitisinone in human milk, the effects on the breastfed infant, or the effects on milk production. Data suggest that nitisinone is present in rat milk due to findings of ocular toxicity and lower body weight seen in drug naive nursing rat pups. The development and health benefits of breastfeeding should be considered along with the mother's clinical need for ORFADIN and any potential adverse effects on the breastfed infant from ORFADIN or from the underlying maternal condition.

8.4 Pediatric Use

The safety and effectiveness of ORFADIN have been established in pediatric patients for the treatment of HT-1 in combination with dietary restriction of tyrosine and phenylalanine. Use of ORFADIN in pediatric patients is supported by evidence from one open-label, uncontrolled clinical study conducted in 207 patients with HT-1 ages 0 to 22 years (median age 9 months) [see Clinical Studies (14)].

8.5 Geriatric Use

Clinical studies of nitisinone did not include any subjects aged 65 and over. No pharmacokinetic studies of nitisinone have been performed in geriatric patients. In general, dose selection for an elderly patient should be cautious reflecting the greater frequency of decreased hepatic, renal, or cardiac function, and concomitant disease or other drug therapy in this patient population.

10 OVERDOSAGE

Accidental ingestion of ORFADIN by individuals eating normal diets not restricted in tyrosine and phenylalanine will result in elevated tyrosine levels. In healthy subjects given a single 1 mg/kg dose of nitisinone, the plasma tyrosine level reached a maximum of 1200 micromol/L at 48 to 120 hours after dosing. After a washout period of 14 days, the mean value of plasma tyrosine was still 808 micromol/L. Fasted follow-up samples obtained from volunteers several weeks later showed tyrosine values back to normal. There were no reports of changes in vital signs or laboratory data of any clinical significance. One patient reported sensitivity to sunlight. Hyper-tyrosinemia has been reported with ORFADIN treatment [see Warnings and Precautions (5.1)].

11 DESCRIPTION

ORFADIN contains nitisinone, which is a hydroxyphenyl-pyruvate dioxygenase inhibitor indicated as an adjunct to dietary restriction of tyrosine and phenylalanine in the treatment of hereditary tyrosinemia type 1 (HT-1).

Nitisinone occurs as white to yellowish-white, crystalline powder. It is practically insoluble in water, soluble in 2M sodium hydroxide and in methanol, and sparingly soluble in alcohol.

Chemically, nitisinone is 2-(2-nitro-4-trifluoromethylbenzoyl) cyclohexane-1,3-dione, and the structural formula is:

Figure 1. The molecular formula is C14H10F3NO5 with a relative mass of 329.23

Capsules: Hard, white-opaque capsule, marked as 2 mg, 5 mg, 10 mg or 20 mg strengths of nitisinone, intended for oral administration. Each capsule contains 2 mg, 5 mg, 10 mg or 20 mg nitisinone, plus pre-gelatinized starch. The capsule shell is gelatin and titanium dioxide and the imprint is an iron oxide.

Oral suspension: 4 mg/mL, a white, slightly viscous opaque suspension. The inactive ingredients are hydroxypropyl methylcellulose, glycerol, polysorbate 80, sodium benzoate, citric acid monohydrate, trisodium citrate dihydrate, strawberry aroma (artificial) and purified water.

Glycerol: Each mL contains 500 mg.

Sodium: Each mL contains 0.7 mg (0.03 mEq).

12 CLINICAL PHARMACOLOGY

12.1 Mechanism of Action

Nitisinone is a competitive inhibitor of 4-hydroxyphenyl-pyruvate dioxygenase, an enzyme upstream of fumarylacetoacetate hydrolase (FAH) in the tyrosine catabolic pathway. By inhibiting the normal catabolism of tyrosine in patients with HT-1, nitisinone prevents the accumulation of the catabolic intermediates maleylacetoacetate and fumarylacetoacetate. In patients with HT-1, these catabolic intermediates are converted to the toxic metabolites succinylacetone and succinylacetoacetate, which are responsible for the observed liver and kidney toxicity. Succinylacetone can also inhibit the porphyrin synthesis pathway leading to the accumulation of 5-aminolevulinate, a neurotoxin responsible for the porphyric crises characteristic of HT-1.

12.2 Pharmacodynamics

In a clinical study, patients with HT-1 were diagnosed by the presence of succinylacetone in urine or plasma and treated with ORFADIN [see Clinical Studies (14)]. In all 186 patients whose urine succinylacetone was measured, the urinary succinylacetone concentration decreased to less than 1 mmol/mol creatinine, the lower limit of quantitation. The median time to normalization of urine succinylacetone was 0.3 months. The probability of recurrence of abnormal values of urine succinylacetone was 1% at a nitisinone concentration of 37 micromol/L (95% confidence interval: 23, 51 micromol/L). In 87% (150/172) of patients whose plasma succinylacetone was measured, the plasma succinylacetone concentration decreased to less than 0.1 micromol/L, the lower limit of quantitation. The median time to normalization of plasma succinylacetone was 3.9 months.

In another study, comparing two dosing regimens, succinylacetone was measured in urine and/or blood in 16 patients with HT-1 aged 5 years to 24 years. All study patients were on a stable ORFADIN daily dosage (0.4 mg/kg/day to 1 mg/kg/day) during both study dosing regimens. After at least 4 weeks of twice daily dosing with ORFADIN, both the urine and/or blood succinylacetone concentrations were below the limit of quantitation for the assay. Patients were then switched to once daily dosing with the same total daily dosage of ORFADIN and blood and/or urine succinylacetone concentrations remained undetectable when measured following at least 4 weeks of treatment with once daily dosing.

Nitisinone inhibits catabolism of the amino acid tyrosine and can result in elevated plasma levels of tyrosine. Therefore, treatment with nitisinone requires restriction of the dietary intake of tyrosine and phenylalanine to prevent the toxicity associated with elevated plasma levels of tyrosine [see Warnings and Precautions (5.1)].

12.3 Pharmacokinetics

The single-dose pharmacokinetics of nitisinone have been studied for both ORFADIN capsules and ORFADIN oral suspension in healthy adult subjects and the multiple-dose pharmacokinetics have been studied for ORFADIN capsules in healthy subjects.

Absorption

The pharmacokinetic characteristics following single oral administration of ORFADIN 30 mg under fasting conditions are shown in Table 3. Compared to ORFADIN capsule, the median Tmax occurred about 3 hours earlier with ORFADIN oral suspension. The multiple-dose characteristics of ORFADIN 80 mg once daily are shown in Table 4. Steady-state (SS) was reached within 14 days dosing in all subjects.

TABLE 3 Nitisinone Arithmetic Mean (CV%) Pharmacokinetic Parameters in Healthy Subjects Following a Single Oral 30 mg Dose of ORFADIN Under Fasting Conditions
Treatment | Cmax (micromol/L) [range] | tmax* (h) [range] | AUC 0-72h (micromol·h/L) [range]
ORFADIN capsule (n=12) | 10.5 (26) | 3.5 | 406 (13)
 |  | [0.8 to 8.0]
ORFADIN oral suspension (n=12) | 10.1 (34) | 0.4 | 350 (17)
 |  | [0.2 to 4.0]
* presented as median [range]

TABLE 4 Nitisinone Arithmetic Mean (CV%) Pharmacokinetic Parameters in Healthy Subjects Following Repeated Once Daily Administration of 80 mg ORFADIN Under Fasting Conditions.
Treatment | Cmax,ss (micromol/L) [CV%] | Cmin,ss (micromol/L) [range] | tmax,ss* (h) [range] | AUC 0-24h,ss (micromol·h/L) [range]
ORFADIN capsule (n=18) | 120 (23) | 73(24) | 4.0 | 2204(18)
 |  |  | [0.0 to 16.0]
* presented as median [range]

Food Effect: No food effect study was conducted with ORFADIN capsules. For ORFADIN oral suspension, a high calorie (800 to 1000 calories) and high fat meal (approximately 50% of total caloric content) did not affect nitisinone total exposure (AUC72h), but decreased the Cmax by approximately 20% [see Dosage and Administration (2.2)].

Distribution

In vitro binding of nitisinone to human plasma proteins is greater than 95% at 50 micromolar concentration.

Elimination

The mean terminal plasma half-life of single dose nitisinone in healthy male subjects is 54 hours. The mean (CV%)apparent plasma clearance in 18 healthy adults following multiple once daily doses of ORFADIN 80 mg is 113 (16) mL/h.

Metabolism: In vitro studies have shown that nitisinone is relatively stable in human liver microsomes with minor metabolism possibly mediated by CYP3A4 enzyme.

Excretion: Renal elimination of nitisinone is of minor importance, since the mean of the fraction of dose excreted as unchanged nitisinone in the urine (fe(%)) was 3.0% (n=3) following multiple oral doses of 80 mg daily in healthy subjects. The estimated mean (CV%) renal clearance of nitisinone was 0.003 L/h (25%).

Drug Interaction Studies

Nitisinone does not inhibit CYP2D6. Nitisinone is a moderate inhibitor of CYP2C9, and a weak inducer of CYP2E1 (Table 5). Nitisinone is an inhibitor of OAT1/3 (Table 5).

Table 5. Percent Change in AUC0-∞ and Cmax for Co-administered Drugs in the Presence of ORFADIN in 18 Healthy Subjects
Co-administered Drug a | Dose of Co-administered Drug (Route of Administration) | Effect of Nitisinone on the Pharmacokinetics of Co-administered Drug b
Co-administered Drug a | Dose of Co-administered Drug (Route of Administration) | AUC 0-∞ | Cmax
CYP2C9 Substrate Tolbutamide c | 500 mg (oral) | 131% ↑ | 16% ↑
CYP2E1 Substrate Chlorzoxazone | 250 mg (oral) | 27% ↓ | 18% ↓
OAT1/3 Substrate Furosemide | 20 mg (intravenous) | 72% ↑ | 12% ↑
↑ = Increased; ↓ = Decreased
a The interacting drug was administered alone on Day 1 and together with ORFADIN on Day 17.
b Multiple doses of 80 mg ORFADIN were administered daily alone from Day 3 to Day 16.
c 16 subjects in Period 2 received ORFADIN and tolbutamide while 18 subjects in Period 1 received ORFADIN alone.

In Vitro Studies Where Drug Interaction Potential Was Not Further Evaluated Clinically

In vitro studies showed that nitisinone does not inhibit CYP1A2, 2C19, or 3A4. Nitisinone does not induce CYP1A2, 2B6 or 3A4/5. Nitisinone does not inhibit P-gp, BCRP, OATP1B1, OATP1B3 and OCT2-mediated transports at therapeutically relevant concentrations.

13 NONCLINICAL TOXICOLOGY

13.1 Carcinogenesis, Mutagenesis, Impairment of Fertility

The carcinogenic potential of nitisinone was assessed in a 26-week oral (gavage) carcinogenicity study in Tg.rasH2 mice. There were no drug-related neoplastic findings in male or female Tg.rasH2 mice at doses up to 100 mg/kg/ day nitisinone (approximately 8.1 times the recommended initial dose of 1 mg/kg/day on a body surface area basis).

Nitisinone was not genotoxic in the Ames test and the in vivo mouse liver unscheduled DNA synthesis (UDS) test. Nitisinone was mutagenic in the mouse lymphoma cell (L5178Y/TK+/-) forward mutation test and in an in vivo mouse bone marrow micronucleus test.

In a single dose-group study in rats given 100 mg/kg (16.2 times the recommended initial dose of 1 mg/kg/day on a body surface area basis), reduced litter size, decreased pup weight at birth, and decreased survival of pups after birth was demonstrated.

14 CLINICAL STUDIES

The efficacy and safety of ORFADIN in patients with HT-1 was evaluated in one open-label, uncontrolled study of 207 patients with HT-1, ages 0 to 22 years at enrollment (median age 9 months). Patients were diagnosed with HT-1 by the presence of succinylacetone in the urine or plasma. All patients were treated with ORFADIN at a starting dose of 0.3 to 0.5 mg/kg twice daily, and the dose was increased in some patients to 1 mg/kg twice daily based on weight, liver and kidney function tests, platelet count, serum amino acids, urinary phenolic acid, plasma and urine succinylacetone, erythrocyte PBG-synthase, and urine 5-ALA. The median duration of treatment was 22 months (range less than 1 month to 80 months). Efficacy was assessed by comparison of survival and incidence of liver transplant to historical controls.

For patients presenting with HT-1 younger than 2 months of age who were treated with dietary restriction and nitisinone, 2- and 4-year survival probabilities were 88% and 88%, respectively. Data from historical controls showed that patients presenting with HT-1 at younger than 2 months of age and treated with dietary restriction alone had 2- and 4-year survival probabilities of 29% and 29%, respectively. For patients presenting with HT-1 between 2 months and 6 months of age who were treated with dietary restriction and nitisinone, 2- and 4-year survival probabilities were 94% and 94%, respectively. Data for historical controls showed that patients presenting with HT-1 between 2 months and 6 months of age treated with dietary restriction alone had 2- and 4-year survival probabilities of 74% and 60%, respectively.

The effects of nitisinone on urine and plasma succinylacetone, porphyrin metabolism, and urinary alpha-1-microglobulin were also assessed in this clinical study.

Porphyria-like crisis were reported in 3 patients (0.3% of cases per year) during the clinical study. This compares to an incidence of 5 to 20% of cases per year expected as part of the natural history of the disorder. An assessment of porphyria-like crises was performed because these events are commonly reported in patients with HT-1 who are not treated with nitisinone.

Urinary alpha-1-microglobulin, a proposed marker of proximal tubular dysfunction, was measured in 100 patients at baseline. The overall median pretreatment level was 4.3 grams/mol creatinine. After one year of treatment in a subgroup of patients (N=100), overall median alpha-1-microglobulin decreased by 1.5 grams/mol creatinine. In patients 24 months of age and younger in whom multiple values were available (N=65), median alpha-1-microglobulin levels decreased from 5.0 to 3.0 grams/mol creatinine (reference value for age less than or equal to 12 grams/mol creatinine). In patients older than 24 months in whom multiple values were available (N=35), median alpha-1-microglobulin levels decreased from 2.8 to 2.0 grams/mol creatinine (reference for age less than or equal to 6 grams/mol creatinine).

The long term effect of nitisinone on hepatic function was not assessed.

16 HOW SUPPLIED/STORAGE AND HANDLING

Capsules: White capsules marked in black with "NTBC" and identified as 2 mg, 5 mg, 10 mg or 20 mg strengths of nitisinone. The capsules are packed in a high density (HD) polyethylene container with a tamper-resistant low density (LD) polyethylene snap-on cap. Each bottle contains 60 capsules.

2 mg white capsules imprinted "NTBC 2 mg" in black ink, NDC 66658-102-60
5 mg white capsules imprinted "NTBC 5 mg" in black ink, NDC 66658-105-60
10 mg white capsules imprinted "NTBC 10 mg" in black ink, NDC 66658-110-60
20 mg white capsules imprinted "NTBC 20 mg" in black ink, NDC 66658-120-60
Store refrigerated at 2° to 8°C (36° to 46°F). Alternatively, patients/caregivers may store ORFADIN capsules at room temperature up to 25°C (77°F) for up to 45 days. If not used within 45 days, discard ORFADIN capsules.

Oral suspension: White, slightly viscous opaque suspension. 1 mL contains 4 mg of nitisinone. The suspension is provided in a 100 mL brown bottle (type III glass) with a white child resistant HDPE screw cap with sealing and tamper evidence. Each bottle contains 90 mL oral suspension.

Oral suspension 4 mg/mL, NDC 66658-204-90

Store refrigerated at 2°C to 8°C (36°F to 46°F) prior to first use. Do not freeze. Store upright.
After first opening, store the product at room temperature (up to 25°C (77°F)) for up to 60 days. If not used within 60 days, discard unused portion. The discard after date should be noted on the bottle

17 PATIENT COUNSELING INFORMATION

Advise the patient to read the FDA-approved patient labeling (Instructions for Use).

Preparation and Administration Instructions [see Dosage and Administration (2.2)]

Preparation of the Oral Suspension

The oral suspension will be dispensed with an oral syringe of appropriate size and a bottle adaptor provided by a pharmacist or other healthcare provider.

Preparing a Bottle Without the Adapter Already Inserted:

- Store the bottle in the refrigerator prior to first use.
- Remove the bottle from the refrigerator. Calculate 60 days from when the bottle is removed from the refrigerator. Write this date as the “Discard after” date on the bottle label.
- Allow the bottle to warm to room temperature (30 to 60 minutes).
- Shake the bottle vigorously for at least 20 seconds until the solid cake at the bottom of the bottle is completely dispersed. Check that there are no particles left at the bottom of the bottle. Foam will form in the bottle.
- Insert the bottle adapter.

Preparing a Bottle With the Adapter Inserted:

- Shake the bottle vigorously for at least 5 seconds. Check that there are no particles left at the bottom of the bottle. Foam will form in the bottle.

Measuring and Administering the Dose

Once the bottle is prepared with the adapter:

1. Use the oral syringe to measure the dose.
2. Keep the bottle upright and insert the oral syringe into the adapter.
3. Carefully turn the bottle upside down with the oral syringe in place. Wait for the foam to rise to the top of the bottle.
4. Pull back on the syringe plunger to withdraw the dose.
5. Leave the syringe in the adapter and turn the bottle upright.
6. Remove the syringe from the adapter by gently twisting it out of the bottle.
7. Dispense the dose into the patient's mouth.
8. Do not remove the bottle adapter.
9. Store the bottle at room temperature (not above 25°C).

Administration of ORFADIN Capsules and Oral Suspension

- Maintain dietary restriction of tyrosine and phenylalanine when taking ORFADIN.
- Capsules: Take at least one hour before, or two hours after a meal. For patients who have difficulty swallowing the capsules and for which the oral suspension is not suitable [see Warnings and Precautions (5.3]), the capsules may be opened and the contents suspended in a small amount of water, formula or apple sauce immediately before use. Or, the oral suspension may be used instead.
- Oral suspension: Take without regard to meals.

Elevated Plasma Tyrosine Levels, Ocular Symptoms, Developmental Delay and Hyperkeratotic Plaques

- Inform patients that inadequate restriction may be associated with ocular signs and symptoms, intellectual disability and developmental delay, and painful hyperkeratotic plaques on the soles and palms. Advise patients and caregivers of the need to maintain dietary restriction of tyrosine and phenylalanine and to report any unexplained ocular, neurologic, or other symptoms promptly to their healthcare provider [see Warnings and Precautions (5.1)].

Risk of Adverse Reactions Due to Glycerol Content of ORFADIN Oral Suspension

Advise patients receiving doses of greater than 20 mL of ORFADIN oral suspension that they may experience headache, upset stomach and diarrhea due to the glycerol component of the formulation and if they develop symptoms to report these to their healthcare provider [see Warnings and Precautions (5.3)].

Manufactured by:
Apotek Produktion & Laboratorier AB, Sweden

Marketed by:
Sobi, Inc
77 Fourth Avenue, 3rd Floor, Waltham, MA 02451-7559

Instructions for Use
ORFADIN (OR-fuh-din)
(nitisinone)
oral suspension
4 mg/mL

Read this Instructions for Use before you start taking ORFADIN oral suspension and each time you get a refill. There may be new information. This information does not take the place of talking to your healthcare provider about your medical condition or your treatment.

Important information about measuring ORFADIN oral suspension:

- Use the oral syringe provided with your ORFADIN oral suspension to make sure you measure the right amount.
- You will be provided with:
  - 1 bottle of ORFADIN oral suspension
  - 1 oral syringe
  - 1 adapter (The adapter may or may not be inserted in your bottle of ORFADIN oral suspension when you receive it.)

Figure A

If the adapter is not inserted in your bottle of ORFADIN oral suspension when you receive it, follow the instructions in “How to prepare a bottle of ORFADIN oral suspension if the adapter is not inserted.”

If the adapter is inserted in your bottle of ORFADIN oral suspension when you receive it, follow the instructions in “How to prepare a dose of ORFADIN oral suspension after the adapter is inserted.”

How to prepare a bottle of ORFADIN oral suspension if the adapter is not inserted:

See “How should I store ORFADIN oral suspension?” for instructions on how to store ORFADIN oral suspension if the adapter is not inserted.

1. Remove the ORFADIN oral suspension bottle from the refrigerator 30 minutes to 1 hour before using it to allow it to reach room temperature.
  ORFADIN oral suspension should be thrown away (discarded) 60 days after it is removed from the refrigerator and the adapter is inserted in the bottle. Write the discard date on the bottle label.

2. Shake the bottle well for at least 20 seconds until the solid cake of particles at the bottom of the bottle is dissolved (See Figure B). Check that there are no particles left at the bottom of the bottle. Foam will form in the bottle.

Figure B

3. Remove the child resistant screw cap by pushing it down firmly and turning it counter-clockwise (See Figure C).

Figure C

4. Place the open bottle upright on a flat surface. Push the ribbed end of the adapter firmly into the neck of the bottle as far as it will go (See Figure D). Replace the child resistant screw cap on the bottle. Do not remove the adapter from the bottle after it is inserted.

Figure D

5. Follow the instructions in “How to prepare a dose of ORFADIN oral suspension after the adapter is inserted.”

How to prepare a dose of ORFADIN oral suspension after the adapter is inserted

See “How should I store ORFADIN oral suspension?” for instructions on how to store ORFADIN oral suspension after the adapter is inserted.

1. Shake the ORFADIN oral suspension bottle well for at least 5 seconds (See Figure E). Check that there are no particles left at the bottom of the bottle. Foam will form in the bottle.

Figure E

2. Remove the child resistant screw cap right away by pushing it down firmly and turning it counter-clockwise (See Figure F).

Figure F

3. Hold the oral syringe in one hand. With your other hand, fully push down (depress) the plunger (See Figure G).

Figure G

4. Keeping the bottle in an upright position, insert the oral syringe firmly into the adapter (See Figure H).

Figure H

5. Carefully turn the bottle upside down with the oral syringe in place (See Figure I). Wait until you can see that the foam is at the top of the bottle to avoid withdrawing bubbles into the syringe.

Figure I

6. Pull back slowly on the oral syringe plunger until the top edge of the black ring is at the line marking the dose prescribed by your healthcare provider (See Figure J). Figure J shows a dose of 1 mL as an example. If you see air bubbles in the oral syringe, fully push in the plunger so that the oral suspension flows back into the bottle. Then, withdraw your prescribed dose of oral suspension.

Figure J

7. Leave the oral syringe in the adapter and turn the bottle to an upright position. Place the bottle onto a flat surface. Remove the oral syringe by gently twisting it out of the bottle (See Figure K). Do not pull straight up on the syringe to remove it from the bottle because this can cause the adapter to come out of the bottle.

Figure K

8. Place the oral syringe in your mouth right away. Slowly push on the plunger until the oral syringe is empty. See Figure L).

Figure L

9. Leave the adapter in the bottle. Put the child resistant screw cap back on the bottle (See Figure M).

Figure M

10. Remove the plunger from the oral syringe barrel. Rinse the oral syringe with water after each use and let it air dry. Do not replace the plunger into the barrel of the oral syringe until ready to use again for your next dose to allow it to dry. Do not throw away the oral syringe.

- Talk to your healthcare provider or pharmacist if you have questions about how to use the oral syringe or if you lose the oral syringe.

How should I store ORFADIN oral suspension?

- Store the ORFADIN oral suspension bottle in an upright position. Keep the oral syringe with your medicine.

Before the adapter is inserted into the bottle:

- If the adapter has not been inserted into the bottle, store ORFADIN oral suspension in the refrigerator between 36°F to 46°F (2°C to 8°C).
- Do not freeze ORFADIN oral suspension.

After the adapter is inserted into the bottle:

- After the adapter has been inserted into the bottle, store ORFADIN oral suspension at room temperature, 77°F (25°C) or below.
- Throw away (discard) ORFADIN oral suspension 60 days after the adapter is inserted in the bottle. You or your pharmacist should write the discard date on the bottle label.

What are the ingredients in ORFADIN oral suspension?

Active ingredient: nitisinone

Inactive ingredients: hydroxypropyl methylcellulose, glycerol, polysorbate 80, sodium benzoate, citric acid monohydrate, trisodium citrate dihydrate, strawberry aroma (artificial) and purified water

This Instructions for Use has been approved by the U.S. Food and Drug Administration.

Manufactured by:
Apotek Produktion & Laboratorier AB, Sweden

Marketed by:
Sobi, Inc
890 Winter Street
Waltham, MA 02451

© Swedish Orphan Biovitrum AB (publ). All rights reserved.

Issued: April 2016

Principal Display Panel - 2 mg Carton Label

60 capsules NDC 66658-102-60

Orfadin® Capsules
(Nitisinone)
2 mg

For Oral Use

sobi

Principal Display Panel - Bottle Label

For Oral Use

Rx only

See Package Insert

Store refrigerated
2-8 °C (36-46 °F)

Manufactured by:

Apotek Produktion & Laboratorier AB,
Sweden

Orfadin® Capsules

(Nitisinone)

2 mg

sobi

NDC 66658-102-60

60 capsules

Marketed by:

Sobi, Inc
890 Winter Street
Waltham, MA 02451

Principal Display Panel - 5 mg Carton Label

60 capsules NDC 66658-105-60

Orfadin® Capsules
(Nitisinone)
5 mg

For Oral Use

sobi

Principal Display Panel - Bottle Label

For Oral Use

Rx only

See Package Insert

Store refrigerated
2-8 °C (36-46 °F)

Manufactured by:

Apotek Produktion & Laboratorier AB,
Sweden

Orfadin® Capsules

(Nitisinone)

5 mg

sobi

NDC 66658-105-60

60 capsules

Marketed by:

Sobi, Inc
890 Winter Street
Waltham, MA 02451

Principal Display Panel - 10 mg Carton Label

60 capsules NDC 66658-110-60

Orfadin® Capsules
(Nitisinone)
10 mg

For Oral Use

sobi

Principal Display Panel - Bottle Label

For Oral Use

Rx only

See Package Insert

Store refrigerated
2-8 °C (36-46 °F)

Manufactured by:

Apotek Produktion & Laboratorier AB,
Sweden

Orfadin® Capsules

(Nitisinone)

10 mg

sobi

NDC 66658-110-60

60 capsules

Marketed by:

Sobi, Inc
890 Winter Street
Waltham, MA 02451

Principal Display Panel - 20 mg Carton Label

60 capsules NDC 66658-120-60

Orfadin® Capsules
(Nitisinone)
20 mg

For Oral Use

sobi

Principal Display Panel - Bottle Label

For Oral Use

Rx only

See Package Insert

Store refrigerated
2-8 °C (36-46 °F)

Manufactured by:

Apotek Produktion & Laboratorier AB,
Sweden

Orfadin® Capsules

(Nitisinone)

20 mg

sobi

NDC 66658-110-60

60 capsules

Marketed by:

Sobi, Inc
890 Winter Street
Waltham, MA 02451